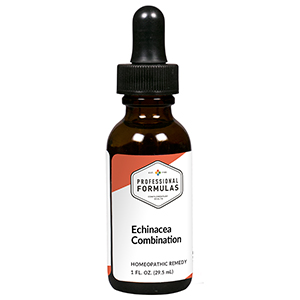 DRUG LABEL: Echinacea Combination
NDC: 63083-9222 | Form: LIQUID
Manufacturer: Professional Complementary Health Formulas
Category: homeopathic | Type: HUMAN OTC DRUG LABEL
Date: 20190815

ACTIVE INGREDIENTS: ECHINACEA ANGUSTIFOLIA WHOLE 2 [hp_X]/29.5 mL; ACONITUM NAPELLUS WHOLE 3 [hp_X]/29.5 mL; ARNICA MONTANA WHOLE 4 [hp_X]/29.5 mL; BAPTISIA TINCTORIA WHOLE 4 [hp_X]/29.5 mL; SANGUINARIA CANADENSIS ROOT 4 [hp_X]/29.5 mL; BRYONIA ALBA ROOT 6 [hp_X]/29.5 mL; EUPATORIUM PERFOLIATUM FLOWERING TOP 6 [hp_X]/29.5 mL; EUPHORBIA RESINIFERA RESIN 6 [hp_X]/29.5 mL; GELSEMIUM SEMPERVIRENS ROOT 6 [hp_X]/29.5 mL; PHYTOLACCA AMERICANA ROOT 6 [hp_X]/29.5 mL; TOXICODENDRON PUBESCENS LEAF 6 [hp_X]/29.5 mL; SILVER NITRATE 8 [hp_X]/29.5 mL; ARSENIC TRIOXIDE 8 [hp_X]/29.5 mL; PHOSPHORUS 8 [hp_X]/29.5 mL; PULSATILLA MONTANA WHOLE 8 [hp_X]/29.5 mL; SULFUR 8 [hp_X]/29.5 mL; THUJA OCCIDENTALIS LEAF 8 [hp_X]/29.5 mL; CALCIUM SULFIDE 10 [hp_X]/29.5 mL; LACHESIS MUTA VENOM 10 [hp_X]/29.5 mL; ZINC 10 [hp_X]/29.5 mL; ARISTOLOCHIA CLEMATITIS ROOT 12 [hp_X]/29.5 mL; HAEMOPHILUS INFLUENZAE 12 [hp_X]/29.5 mL; MERCURIC CHLORIDE 12 [hp_X]/29.5 mL; CORTISONE ACETATE 13 [hp_X]/29.5 mL; STAPHYLOCOCCUS AUREUS 18 [hp_X]/29.5 mL; STREPTOCOCCUS PYOGENES 18 [hp_X]/29.5 mL; RANCID BEEF 199 [hp_X]/29.5 mL
INACTIVE INGREDIENTS: ALCOHOL; WATER

R222

ACTIVE INGREDIENTS

Echinacea angustifolia 2X
Aconitum napellus 3X
Arnica montana 4X
Baptisia tinctoria 4X
Sanguinaria canadensis 4X
Bryonia 6X
Eupatorium perfoliatum 6X
Euphorbium officinarum 6X
Gelsemium sempervirens 6X
Phytolacca decandra 6X
Rhus toxicodendron 6X
Argentum nitricum 8X
Arsenicum album 8X
Phosphorus 8X
Pulsatilla 8X
Sulphur 8X
Thuja occidentalis 8X
Hepar sulphuris calcareum 10X
Lachesis mutus 10X
Zincum metallicum 10X
Aristolochia clematitis 12X
Influenzinum 12X
Mercurius corrosivus 12X
Cortisone aceticum 13X
Staphylococcinum 18X
Streptococcinum 18X
Pyrogenium 199X

QUESTIONS

Professional Formulas

PO Box 2034 Lake Oswego, OR 97035

INDICATIONS

For the temporary relief of cold- and flu-like symptoms such as chills, muscle aches, cough, congestion, runny nose, occasional headache, or fatigue.*

PURPOSE

*Claims based on traditional homeopathic practice, not accepted medical evidence. Not FDA evaluated.

WARNINGS

Persistent symptoms may be a sign of a serious condition. If symptoms persist or are accompanied by a fever, rash, or persistent headache, consult a doctor. Keep out of the reach of children. In case of overdose, get medical help or contact a poison control center right away. If pregnant or breastfeeding, ask a healthcare professional before use.

Keep out of the reach of children.

PREGNANCY OR BREAST FEEDING

If pregnant or breastfeeding, ask a healthcare professional before use.

DIRECTIONS

Place drops under tongue 30 minutes before/after meals. Adults and children 12 years and over: Take 10 drops up to 3 times per day. Consult a physician for use in children under 12 years of age.

OTHER INFORMATION

Tamper resistant. If seal is broken, do not use. After opening, close container tightly and store at room temperature away from heat.

INACTIVE INGREDIENTS

40% ethanol, purified water.

LABEL

Est 1985

Professional Formulas

Complementary Health

Echinacea Combination

Homeopathic Remedy

1 FL. OZ. (29.5 mL)